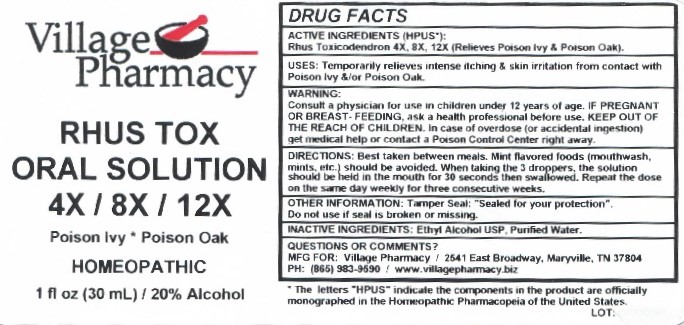 DRUG LABEL: Rhus Tox 4X, 8X, 12X
NDC: 66096-731 | Form: LIQUID
Manufacturer: OHM PHARMA INC.
Category: homeopathic | Type: HUMAN OTC DRUG LABEL
Date: 20180119

ACTIVE INGREDIENTS: TOXICODENDRON PUBESCENS LEAF 4 [hp_X]/30 mL
INACTIVE INGREDIENTS: WATER; ALCOHOL

RHUS TOX 4X, 8X, 12X

ACTIVE INGREDIENTS (HPUS*):

Rhus Toxicodendron 4X, 8X, 12X (Relieves Poison Ivy & Posion Oak).

INDICATIONS AND USAGE

USES: Temporarily relieves intense itching & skin irritation from contact with Poison Ivy & /or Poison Oak.

PURPOSE

(Relieves Poison Ivy & Poison Oak)

DOSAGE AND ADMINISTRATION

DIRECTIONS: Best taken between meals. Mint flavored foods (mouthwash, mints, etc.) should be avoided. When taking the 3 droppers, the solution should be held in the mouth for 30 seconds then swallowed. Repeat the dose on the same day weekly for three consectutive weeks.

WARNINGS:

Consult a physician for use in children under 12 years of age.

IF PREGNANT OR BREAST-FEEDING, ask a health care professional before use.

KEEP OUT OF THE REACH OF CHILDREN. In case of overdose (or accidental ingestion) get medical help or contact a Poison Control Center right away.

KEEP OUT OF THE REACH OF CHILDREN.

INACTIVE INGREDIENTS: Ethyl Alcohol USP, Purified Water.

QUESTIONS & COMMENTS?:

MFG FOR: Village Pharmacy / 2541 East Broadway, Maryville, TN 37804

PH: (865) 983-9590 / www.villagepharmacy.biz

OTHER INFORMATION: Tamper Seal; "Sealed for your protection".

Do not use if seal is broken or missing.

*The letters "HPUS" indicater that the components in this product are officially monographed in the Homeopathic

Pharmacopeiaof the United States.

** Claims based on traditional homeoplathic practice, not accepted medical evidence. Not FDA eveluated.

PACKAGE LABEL

Village Pharmacy

NDC: 66096-731-02

RHUS TOX

ORAL SOLUTION

4X, 8X, 12X

Poison Ivy * Poison Oak

HOMEOPATHIC

1 fl oz (30 mL) / 20% Alcohol